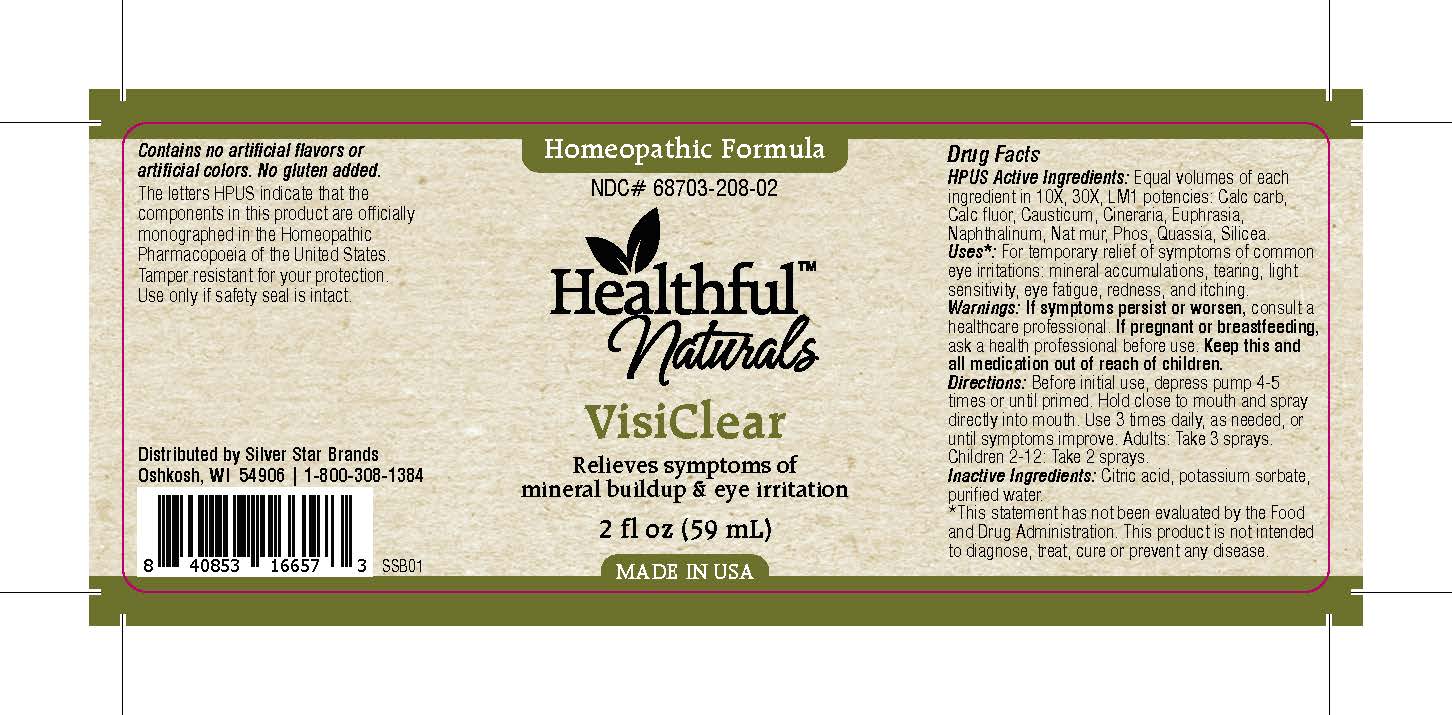 DRUG LABEL: VisiClear
NDC: 68703-208 | Form: SPRAY
Manufacturer: Silver Star Brands
Category: homeopathic | Type: HUMAN OTC DRUG LABEL
Date: 20151110

ACTIVE INGREDIENTS: JACOBAEA MARITIMA 10 [hp_X]/59 mL; EUPHRASIA STRICTA 10 [hp_X]/59 mL; NAPHTHALENE 10 [hp_X]/59 mL; CAUSTICUM 10 [hp_X]/59 mL; OYSTER SHELL CALCIUM CARBONATE, CRUDE 10 [hp_X]/59 mL; CALCIUM FLUORIDE 10 [hp_X]/59 mL; SODIUM CHLORIDE 10 [hp_X]/59 mL; PHOSPHORUS 10 [hp_X]/59 mL; QUASSIA AMARA WOOD 10 [hp_X]/59 mL; SILICON DIOXIDE 10 [hp_X]/59 mL
INACTIVE INGREDIENTS: WATER; ANHYDROUS CITRIC ACID; POTASSIUM SORBATE

Healthful™ Naturals VisiClear

HPUS Active Ingredients

Equal volumes of each ingredient in 10X, 30X, LM1 potencies: Calc carb, Calc fluor, Causticum, Cineraria, Euphrasia, Naphthalinum, Nat mur, Phos, Quassia, Silicea.

Uses

*For temporary relief of symptoms of common eye irritations: mineral accumulations, tearing, light sensitivity, eye fatigue, redness, and itching. *This statement has not been evaluated by the Food and Drug Administration. This product is not intended to diagnose, treat, cure or prevent any disease.

Warnings

If symptoms persist or worsen, consult a healthcare professional. If pregnant or breastfeeding, ask a health professional before use. Keep this and all medication out of reach of children.

Directions

Before initial use, depress pump 4-5 times or until primed. Hold close to mouth and spray directly into mouth. Use 3 times daily, as needed, or until symptoms improve. Adults: Take 3 sprays. Children 2-12: Take 2 sprays.

Other Information

Contains no artificial flavors or artificial colors. No gluten added. The letters HPUS indicate that the components in this product are officially monographed in the Homeopathic Pharmacopoeia of the United States. Tamper resistant for your protection. Use only if safety seal is intact.

INACTIVE INGREDIENT

Citric acid, potassium sorbate, purified water.

KEEP OUT OF REACH OF CHILDREN

Keep this and all medication out of reach of children.

PREGNANCY OR BREAST FEEDING

If pregnant or breastfeeding, ask a health professional before use.

PURPOSE

Relieves symptoms of mineral buildup & eye irritation